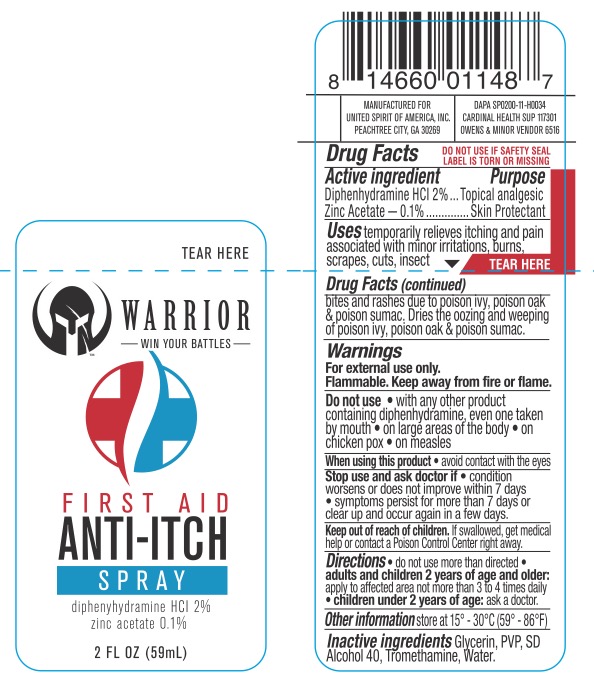 DRUG LABEL: Warrior First Aid Anti Itch
NDC: 72839-647 | Form: SPRAY
Manufacturer: Derma Care Research Labs, LLC
Category: otc | Type: HUMAN OTC DRUG LABEL
Date: 20241220

ACTIVE INGREDIENTS: DIPHENHYDRAMINE HYDROCHLORIDE 2 g/100 mL; ZINC ACETATE 0.1 g/100 mL
INACTIVE INGREDIENTS: ALCOHOL; TROMETHAMINE; GLYCERIN; WATER; POVIDONE

Warrior First Aid Anti Itch Spray, Diphenhydramine HCl 2%, Zinc Acetate 0.1%

ACTIVE INGREDIENT

Diphenhydramine HCl 2%, Zinc Acetate 0.1%

PURPOSE

Topical Analgesic, Skin Protectant

INDICATIONS AND USAGE

For the temporary relief of pain and itching associated with insect bites, minor burns, sunburn, minor cuts, scrapes, minor skin irritations, and rashes due to poison ivy, oak, and sumac. Dries the oozing and weeping of poison ivy, oak, and sumac.

WARNINGS

For external use only. Flammable--Keep away from fire or flame. Do not use on chicken pox, on large areas of the body, with any other products containing diphenhydramine, even one taken by mouth. When using this product avoid contact with eyes. In case of contact with eyes, flush thoroughly with water. Contents under pressure. Do not puncture or incinerate. Do not store at temperature above 120F. . Stop use and ask a doctor if condition worsens, if symptoms persist for more than 7 days or clear up and occur again within a few days.

KEEP OUT OF REACH OF CHILDREN

If swallowed, get medical help or contact a Poison Control Center right away.

Do not use more than directed. Adults and children 2 years of age and older, apply to the affected area not more than 3 to 4 times daily. Children under 2 years of age: ask a doctor.

INACTIVE INGREDIENT

Glycerin, PVP, SD Alcohol, 40, Tromethamine, Water.